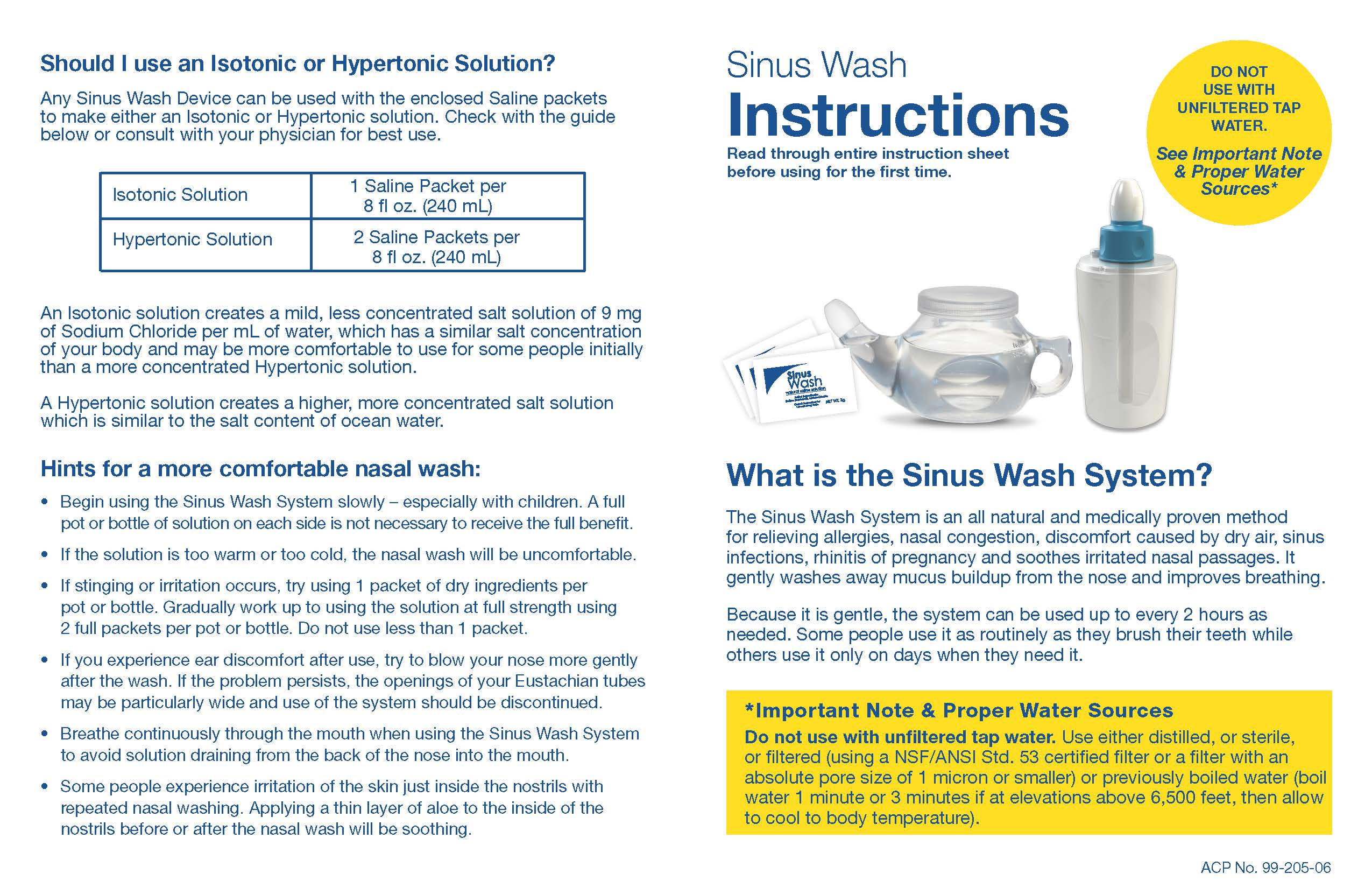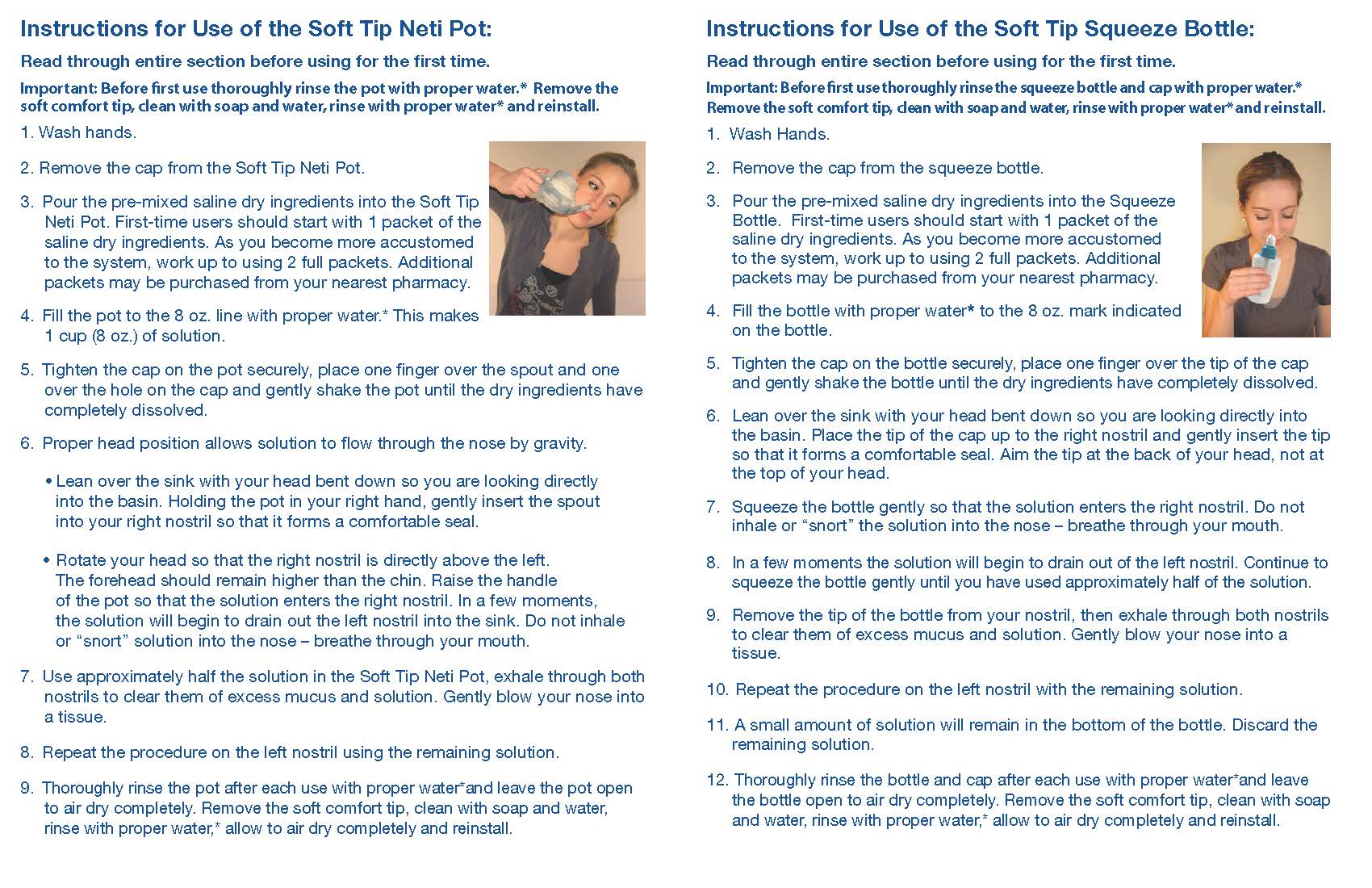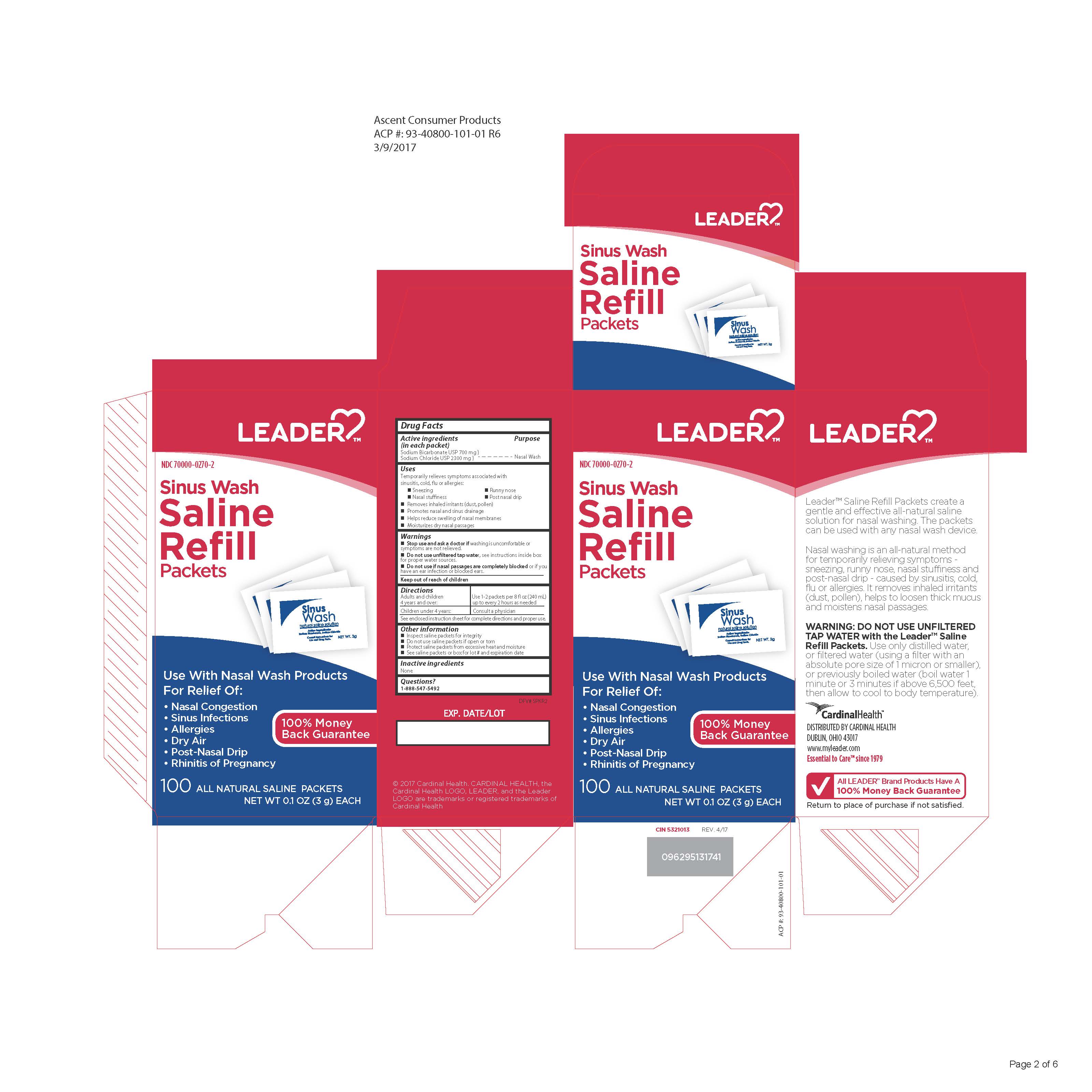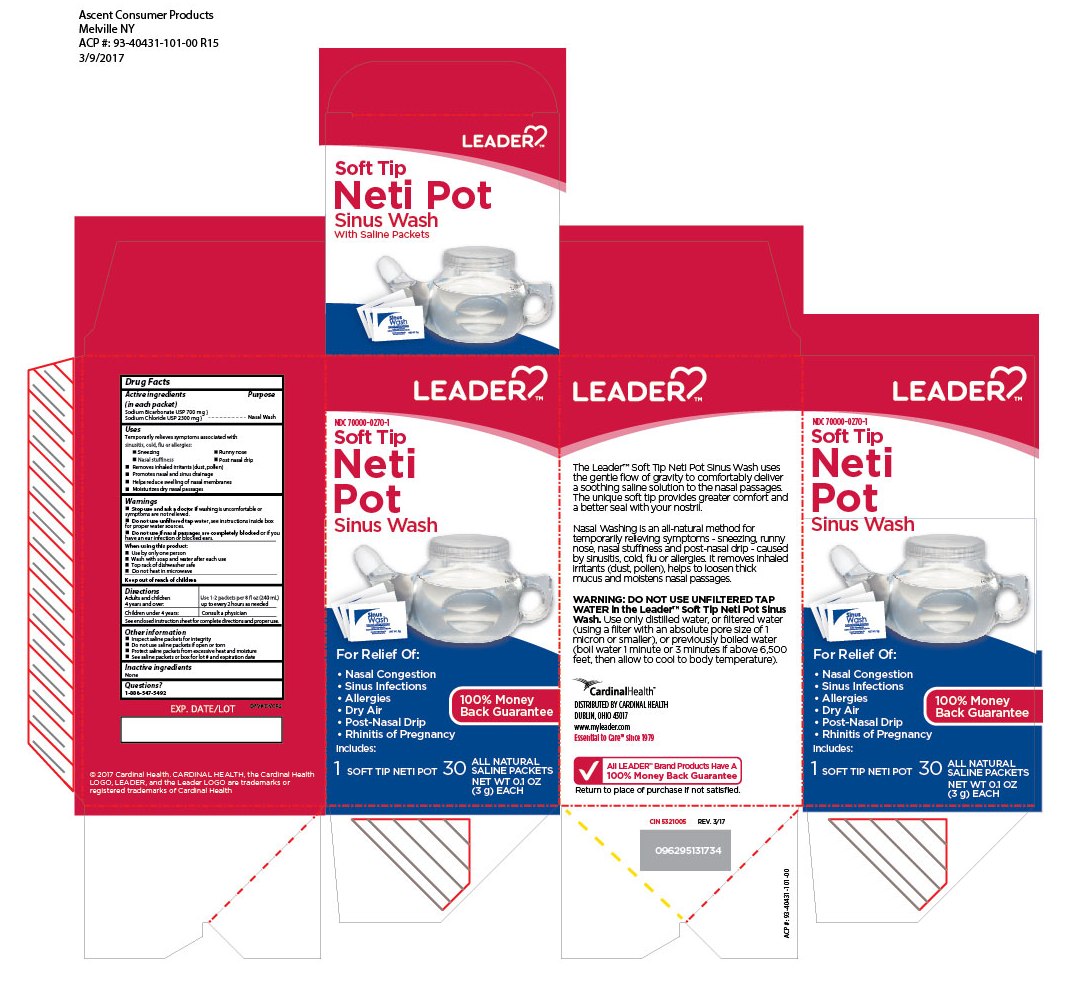 DRUG LABEL: Leader Sinus Wash Saline Refill Packets
NDC: 70000-0270 | Form: POWDER, FOR SOLUTION
Manufacturer: Cardinal Health, 110 dba LEADER
Category: otc | Type: HUMAN OTC DRUG LABEL
Date: 20250709

ACTIVE INGREDIENTS: SODIUM BICARBONATE 700 mg/3 g; SODIUM CHLORIDE 2300 mg/3 g
INACTIVE INGREDIENTS: WATER

Leader 100ct Refills

Active Ingredients

(in each packet)

Sodium Bicarbonate USP 700 mg

Sodium Chloride USP 2300 mg

Purpose

Nasal Wash

Uses

Temporarily relieves symptoms associated with sinusitis, cold, flu or allergies:

•Sneezing •Runny nose

•Nasal stuffiness •Post nasal drip

•Removes inhaled irritants (dust, pollen)

•Promotes nasal and sinus drainage

•Helps reduce swelling of nasal membranes

•Moisturizes dry nasal passages

Keep out of reach of children

Warnings

• Stop use and ask a doctor if washing is uncomfortable or symptoms are not relieved.

• Do not use unfiltered tap water, see instructions inside box for for proper water sources.

• Do not use if nasal passages are completely blocked or if you have an ear infection or blocked ears.

DOSAGE AND ADMINISTRATION

Directions; Adults and children; 4 years and over: | Use 1-2 packets per 8 fl oz(240 mL); up to every 2 hours as needed
Children under 4 years: | Consult a physician
See enclosed instruction sheetfor complete directions and proper use

Other information

- Inspect saline packets for integrity
- Do not use saline packets if open or torn
- Protect saline packets from excessive heat and moisture
- See saline packets or box for lot # and expiration date

Questions?

1-888-547-5492

Inactive Ingredients

None